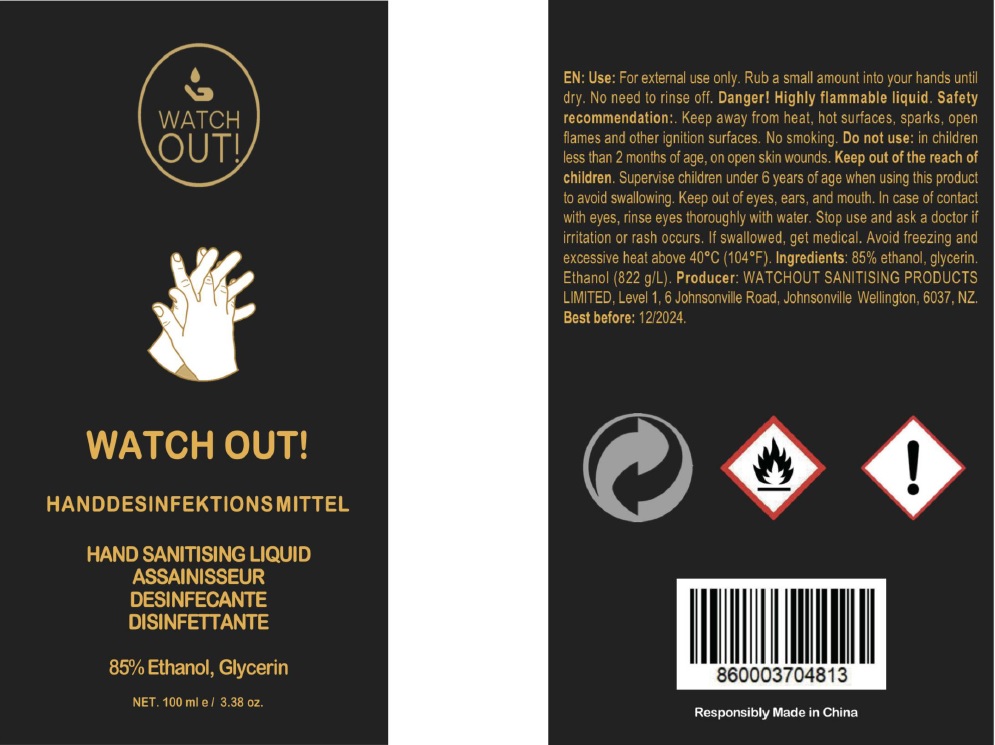 DRUG LABEL: Alcohol Disinfectant
NDC: 76718-004 | Form: SOLUTION
Manufacturer: Guangzhou Jukang Sanitary Products Co., Ltd.
Category: otc | Type: HUMAN OTC DRUG LABEL
Date: 20200717

ACTIVE INGREDIENTS: ALCOHOL 85 mL/100 mL
INACTIVE INGREDIENTS: WATER; GLYCERIN

Active ingredient

Ethanol 85%

Purpose

Antiseptic

Use

For hand-washing to decrease bacteria on the skin.

KEEP OUT OF REACH OF CHILDREN

supervise children under 6 years of age when using this product to avoid swallowing. If swallowed get medical.

warnings:

For external use only

Danger! Highly flammable liquid. Safety recoommended: Keep away from heat, hot surfaces, sparks, open flames and other ignition surfaces. No smoking.

Do not use: in children less than 2 months of age, on open skin wounds.

When using this product, Keep out of eyes, ears, and mouth. In case of contact with eyes, rinse eyes thoroughly with eater

Stop use and ask a doctor if irritation and rash occurs.

Avoid freezing and excessive heat above 40℃ (104℉)

DOSAGE AND ADMINISTRATION

rub a small amount into your hands until dry, No need to rinse off.

Inactive ingredients

glycerin, water